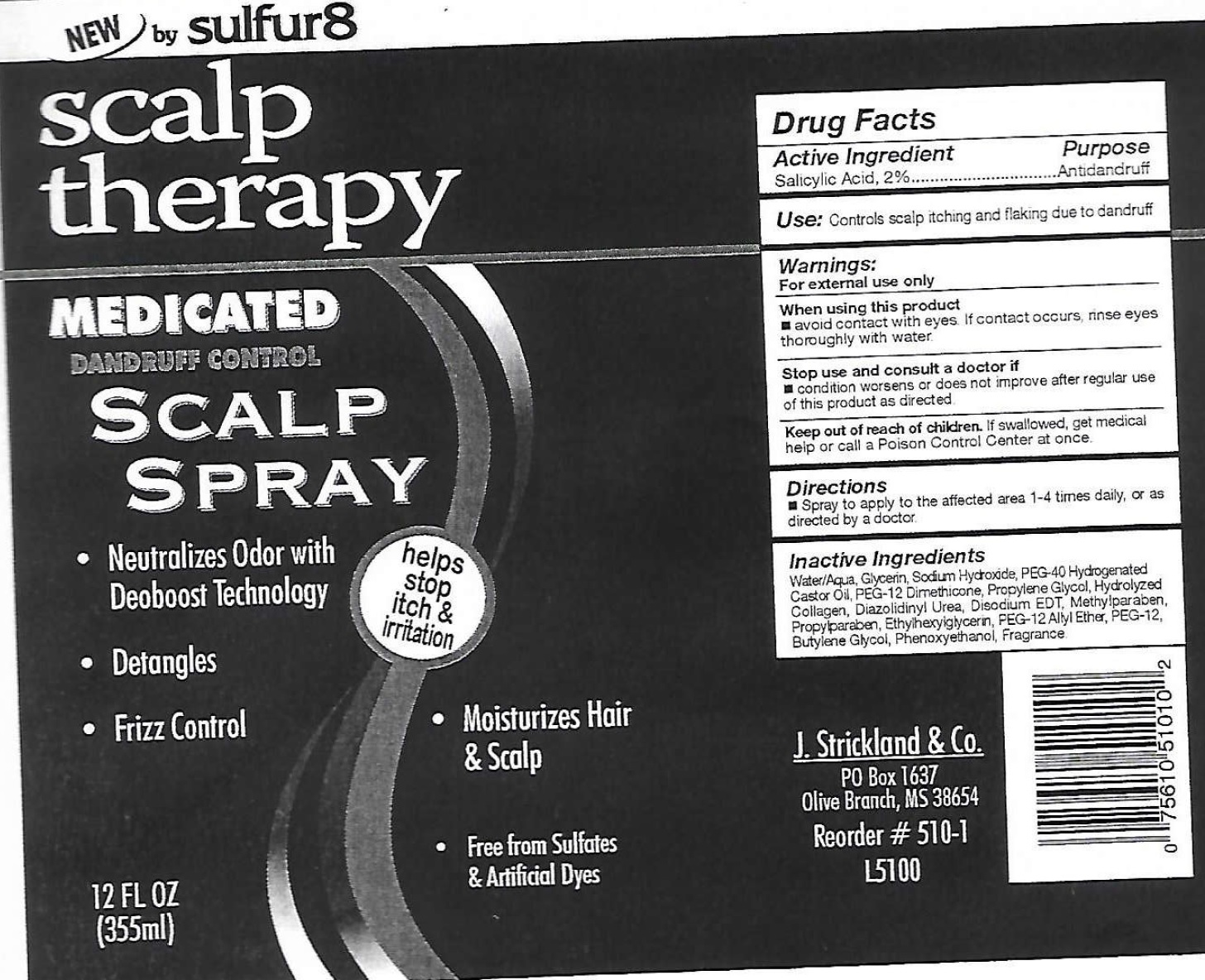 DRUG LABEL: Sulfur 8 Scalp Therapy Medicated Dandruff Control
NDC: 12022-032 | Form: SPRAY
Manufacturer: J. Strickland and Co.
Category: otc | Type: HUMAN OTC DRUG LABEL
Date: 20231021

ACTIVE INGREDIENTS: SALICYLIC ACID 20 mg/1 mL
INACTIVE INGREDIENTS: WATER; GLYCERIN; SODIUM HYDROXIDE; PEG-12 DIMETHICONE (300 CST); PROPYLENE GLYCOL; DIAZOLIDINYL UREA; EDETATE DISODIUM ANHYDROUS; METHYLPARABEN; PROPYLPARABEN; ETHYLHEXYLGLYCERIN; POLYETHYLENE GLYCOL 600; BUTYLENE GLYCOL; PHENOXYETHANOL

Sulfur 8 Scalp Therapy Medicated Dandruff Control Scalp Spray

Active Ingredient

Salicylic Acid, 2%

Purpose

Antidandruff

Use:

Controls scalp itching and flaking due to dandruff

Warnings

For external use only

When using this product

avoid contact with eyes. If contact, rinse eyes thoroughly with water.

Stop use and consult a doctor if

condition worsens or does not improve after regular use of this product as directed.

Keep out of reach of children.

If swallowed, get medical help or call a Poison Control Center at once.

Directions

Spray to apply to the affected area 1-4 times daily, or as directed by a doctor

Inactive Ingredients

Water, Glycerin, Sodium Hydroxide, PEG-40 Hydrogenate Castor Oil, PEG-12 Dimethicone, Propylene Glycol, Hydrolyzed Collagen, Diazolidinyl Urea, Disodium EDT, Methylparaben, Propylparaben, Ethylhexylglycerin, PEG-12 Alyl Ether, PEG-12, Butylene Glycol, Phenoxyethanol, Fragrance